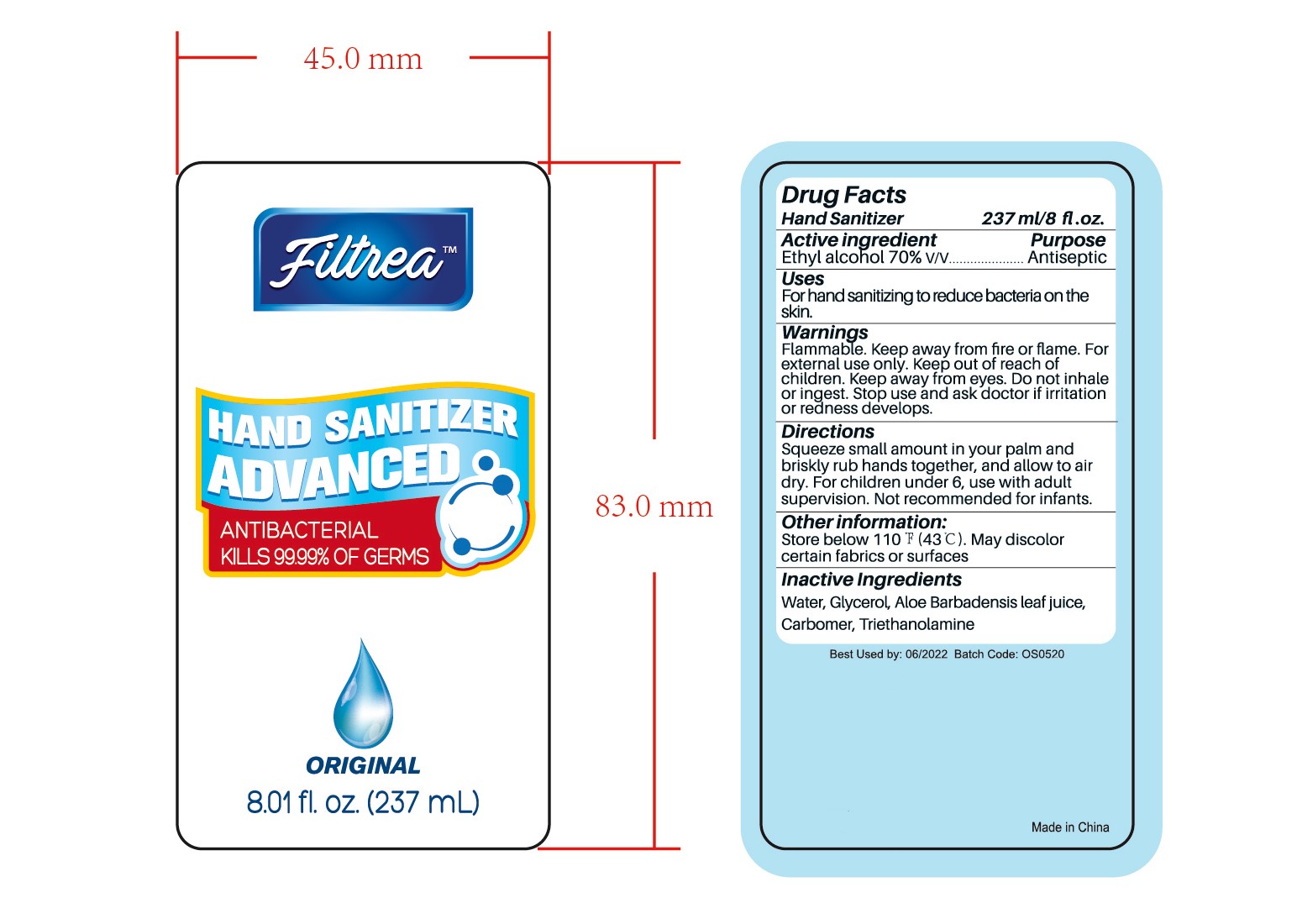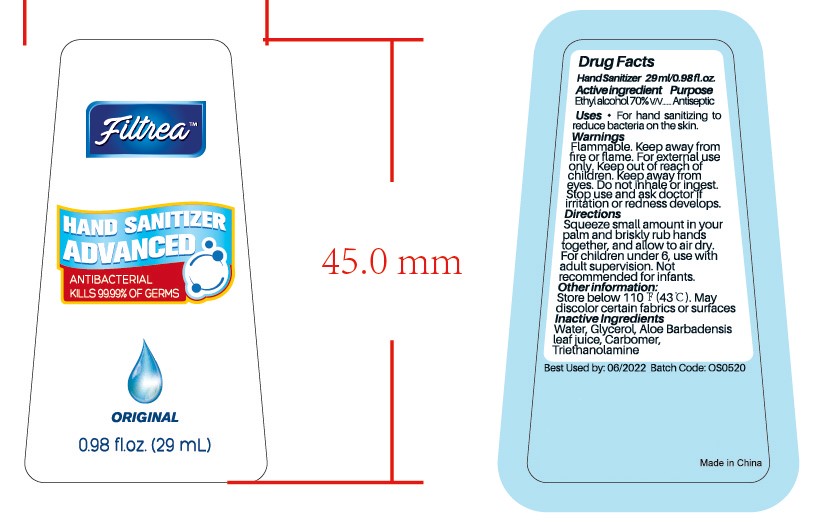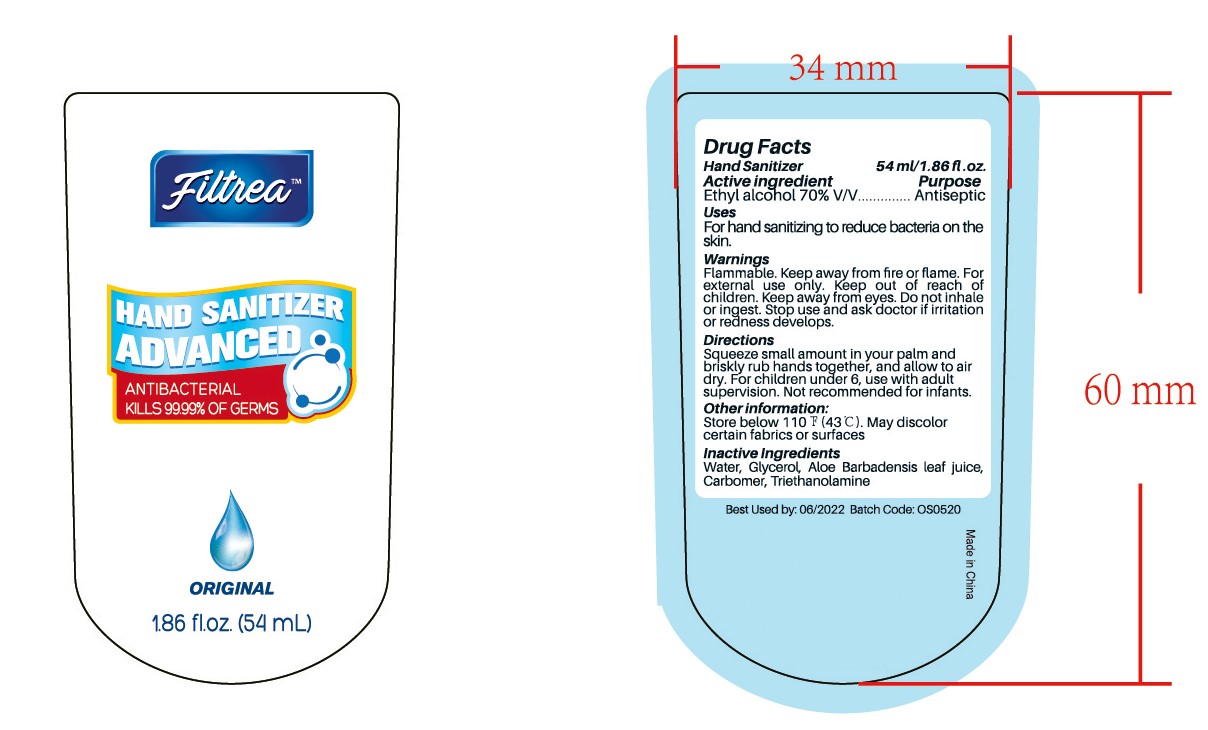 DRUG LABEL: HAND SANITIZER
NDC: 47993-310 | Form: GEL
Manufacturer: NINGBO JIANGBEI OCEAN STAR TRADING CO.,LTD
Category: otc | Type: HUMAN OTC DRUG LABEL
Date: 20201105

ACTIVE INGREDIENTS: ALCOHOL 70 mL/100 mL
INACTIVE INGREDIENTS: WATER; GLYCERIN; ALOE VERA LEAF; CARBOMER 940; TRIETHANOLAMINE BENZOATE

47993-310

Active ingredients

Ethyl alcohol 70% V/V

PURPOSE

Antiseptic

Uses：

For hand sanitizing to reduce bacteria on the skin.

Warnings:

Flammable. Keep away from fire or flame.For external use only.

Keep out of reach of children.

WHEN USING

Keep away from eyes. Do not inhale or ingest.

Stop use and ask doctor if irritation or redness develops.

Directions:

Squeeze small amount in your palm and briskly rub hands together, and allow to air dry. For children under 6, use with adult supervision. Not recommended for infants.

Other information:

Store below 110℉(43℃).May discolor certain fabrics or surface.

Inactive Ingredients:

Water,Glycerol,Aloe barbadensis leaf juice,Carbomer,Triethanolamine